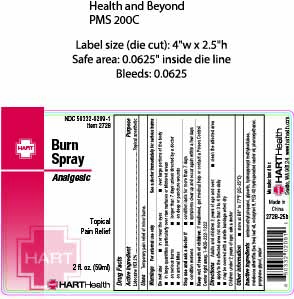 DRUG LABEL: Burn
NDC: 50332-0209 | Form: SPRAY
Manufacturer: HART Health
Category: otc | Type: HUMAN OTC DRUG LABEL
Date: 20250815

ACTIVE INGREDIENTS: LIDOCAINE HYDROCHLORIDE 2 mg/100 mL
INACTIVE INGREDIENTS: AMINOMETHYL PROPANOL; GLYCERIN; HYDROXYPROPYL METHYLCELLULOSE; MELALEUCA ALTERNIFOLIA (TEA TREE) LEAF OIL; OCTOXYNOL 9; PEG-40 HYDROGENATED CASTOR OIL; PHENOXYETHANOL; PROPYLENE GLYCOL; WATER

Burn Spray

Active Ingredients:

Lidocaine HCL 2%

Purpose:

Topical Anesthetic

Uses:

Temporary pain relief of minor burns

Warnings

For external use only

See a doctor immediately or serious burns

Do not use

- in or near the eyes
- over large portions of the body
- in large quantities particularly over raw surfaces or blistered areas
- on serious burns
- longer than 7 days unless directed by a doctor
- on animal bites
- on deep or puncture wounds

Stop use and ask a doctor if

- condition lasts for more than 7 days
- condition worsens
- symptoms clear up and occur again within a few days

Keep out of reach of children.

If swallowed, get medical help or contact a Poison Control Center right away. 1-800-222-1222

Directions:

Adults and children 2 years of age and over:

- clean the affected area
- apply to the affected area not more than 3 to 4 times dailys
- may be covered with a sterile bandage when dry

Children under 2 years of age: ask a doctor

OTHER SAFETY INFORMATION

store at 68° to 77°F (20-25°C)

Inactive Ingredients

aminomethyl propanol, glycerin, hydroxypropyl methylcellulose, melaleuca alterniflia (tea tree) leaf oil, octoxynol 9, PEG-40 hydrogenated castor oil, phenoxyethanol, propylene glycol, water